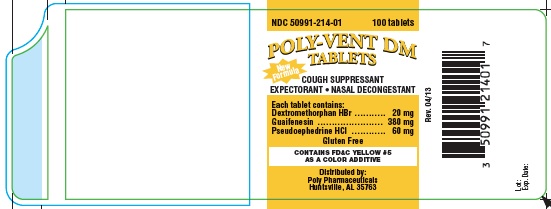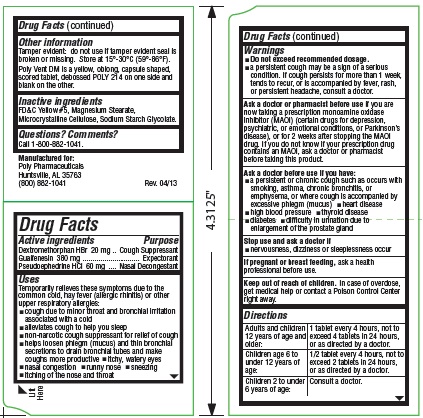 DRUG LABEL: Poly-Vent DM
NDC: 50991-214 | Form: TABLET
Manufacturer: Poly Pharmaceuticals, Inc.
Category: otc | Type: HUMAN OTC DRUG LABEL
Date: 20251219

ACTIVE INGREDIENTS: PSEUDOEPHEDRINE HYDROCHLORIDE 60 mg/1 1; GUAIFENESIN 380 mg/1 1; DEXTROMETHORPHAN HYDROBROMIDE 20 mg/1 1
INACTIVE INGREDIENTS: FD&C YELLOW NO. 5; MAGNESIUM STEARATE; CELLULOSE, MICROCRYSTALLINE; SODIUM STARCH GLYCOLATE TYPE A POTATO

Poly-Vent DM Tablets

Drug Facts

Active ingredients

Dextromethorphan HBr 20mg
Guaifenesin 380mg
Pseudoephedrine HCl 60mg

Purpose

Cough Suppressant

Expectorant

Nasal Decongestant

Uses

Temporarily relieves these symptoms due to the common cold, hay fever (allergic rhinitis) or other upper respiratory allergies:

- cough due to minor throat and bronchial irritation associated with a cold
- alleviates cough to help you sleep
- non-narcotic cough suppressant for relief of cough
- helps loosen phlegm (mucus) and thin bronchial secretions to drain bronchial tubes and make coughs more productive
- itchy, watery eyes
- nasal congestion
- runny nose
- sneezing
- itching of the nose and throat

Warnings

- Do not exceed recommended dosage.
- a persistent cough may be a sign of a serious condition. If cough persists for more than 1 week, tends to recur, or is accompanied by fever, rash, or persistent headache, consult a doctor.

Ask a doctor or pharmacist before use

if you are now taking a prescription monoamine oxidase inhibitor (MAOI) (certain drugs for depression, psychiatric, or emotional conditions, or Parkinson’s disease), or for 2 weeks after stopping the MAOI drug. If you do not know if your prescription drug contains an MAOI, ask a doctor or pharmacist before taking this product.

Ask a doctor before use if you have:

- a persistent or chronic cough such as occurs with smoking, asthma, chronic bronchitis, or emphysema, or where cough is accompanied by excessive phlegm (mucus)
- heart disease
- high blood pressure
- thyroid disease
- diabetes
- difficulty in urination due to enlargement of the prostate gland

Stop use and ask a doctor if:

- nervousness, dizziness, or sleeplessness occur

If pregnant or breast feeding,

ask a health professional before use.

Keep out of reach of children.

In case of overdose, get medical help or contact a Poison Control Center right away.

Directions

Adults and children 12 years of age and over: | 1 tablet every 4 hours, not to exceed 4 tablets in 24 hours, or as directed by a doctor.
Children age 6 to under 12 years of age: | ½ tablet every 4 hours, not to exceed 2 tablets in 24 hours, or as directed by a doctor.
Children 2 to under 6 years of age: | Consult a doctor.

Other information

Tamper evident: do not use if tamper evident seal is broken or missing. Store at 15°-30°C (59°-86°F).

Poly Vent DM is a yellow, oblong, capsule shaped, scored tablet, debossed POLY 214 on one side and

blank on the other.

Inactive ingredients

FD&C Yellow #5, Magnesium Stearate, Microcrystalline Cellulose, Sodium Starch Glycolate.

Questions? Comments?

Call 1-800-882-1041.

Manufactured for:
Poly Pharmaceuticals
Quitman, MS 39355
(800) 882-1041 Rev. 04/13

PRINCIPAL DISPLAY PANEL

NDC 50991-214-01
Poly-Vent DM Tablets
Cough Suppressant
Expectorant ● Nasal Decongestant
100 tablets